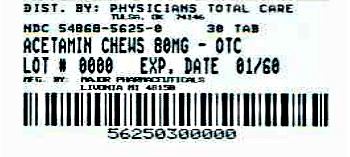 DRUG LABEL: Acetaminophen
NDC: 54868-5625 | Form: TABLET, CHEWABLE
Manufacturer: Physicians Total Care, Inc.
Category: otc | Type: HUMAN OTC DRUG LABEL
Date: 20120606

ACTIVE INGREDIENTS: ACETAMINOPHEN 80 mg/1 1
INACTIVE INGREDIENTS: ASPARTAME; SILICON DIOXIDE; HYPROMELLOSES; MAGNESIUM STEARATE; MANNITOL; POVIDONE; STARCH, CORN; SODIUM CHLORIDE; SODIUM STARCH GLYCOLATE TYPE A POTATO; SORBITOL; STEARIC ACID; SUCRALOSE

Drug Facts

Active Ingredient (in each chewable tablet)

Acetaminophen 80 mg

Purposes

Pain Reliever/Fever Reducer

Uses

Temporarily relieves minor aches and pain due to:

■ The common cold ■ Flu ■ Headache ■ Sore throat

■ Toothache

Temporarily reduces fever.

Warnings

Liver warning: This product contains acetaminophen. Severe liver damage may occur if your child takes ■ more than 5 doses in 24 hours, which is the maximum daily amount ■ with other drugs containing acetaminophen.

WARNINGS

Sore throat warning: If sore throat is severe, persists for more than 2 days, is accompanied or followed by fever, headache, rash, nausea, or vomiting, consult a doctor promptly.

Do not use ■ with any other other drug containing acetaminophen (prescription or non prescription). If you are not sure whether a drug contains acetaminophen, ask a doctor or pharmacist.
■ if your child is allergic to acetaminophen or any of the inactive ingredients in this product.

Ask a doctor before use if your child has liver disease.

Ask a doctor or pharmacist before use if your child is taking the blood thinning drug warfarin.

When using this product: Do not exceed recommended dose.

Stop use and ask a doctor if ■ Pain gets worse or lasts more than 5 days ■ Fever gets worse or lasts more than 3 days ■ New symptoms occur ■ Redness or swelling is present

These could be signs of a serious condition.

Keep out of reach of children.

OVERDOSAGE

Overdose warning: Taking more than the recommended dose (overdose) may cause liver damage. In the case of overdose, get medical help or contact a Poison Control Center right away. (1-800- 222-1222). Quick medical attention is critical even if you do not notice any signs or symptoms.

Directions

■ This products does not contain directions or complete warnings for adult use.
■ Find right dose on the chart below. If possible, use weight to dose; otherwise, use age.
■ Chew before swallowing
■ If needed, repeat dose every 4 hours while symptoms lasts
■ Do not give more than 5 times in 24 hours
■ Do not give for more than 5 days unless directed by a doctor.

Weight | Age | Tablets
Under 24 lbs | Under 2 years | Ask a doctor
24-35 lbs | 2-3 years | 2 tablets
36-47 lbs | 4-5 years | 3 tablets
48-59 lbs | 6-8 years | 4 tablets
60-71 lbs | 9-10 years | 5 tablets
72-95 lbs | 11 years | 6 tablets

Other Information

- Phenylketonurics: Contain Phenylalanine 14 mg per tablet
- Do not use if imprinted safety seal under cap is broken or missing
- Store at room temperature in a dry place

Inactive Ingredients

Aspartame, Colloidal Silica, D&C Red # 27 Lake, Hypromellose, Magnesium Stearate, Mannitol, Natural & Artificial Berry Flavors, Povidone, Pregelatinized Starch, Sodium Chloride, Sodium Starch Glycolate, Sorbitol, Stearic Acid and Sucralose.

Questions?

Adverse Drug Event Call: (800) 616-2471

Principal Display Panel

NDC 54868-5625-0
*Compare to the active ingredient in Children's Chewable Tylenol®
Children's Chewable

AGES 2-6

Acetaminophen Chewable Tablets

30 Tablets, 80 mg EACH

Fever reducer/ Pain reliever
ASPIRIN FREE ● IBUPROFEN FREE

See New Warnings Information

Fruit Flavor